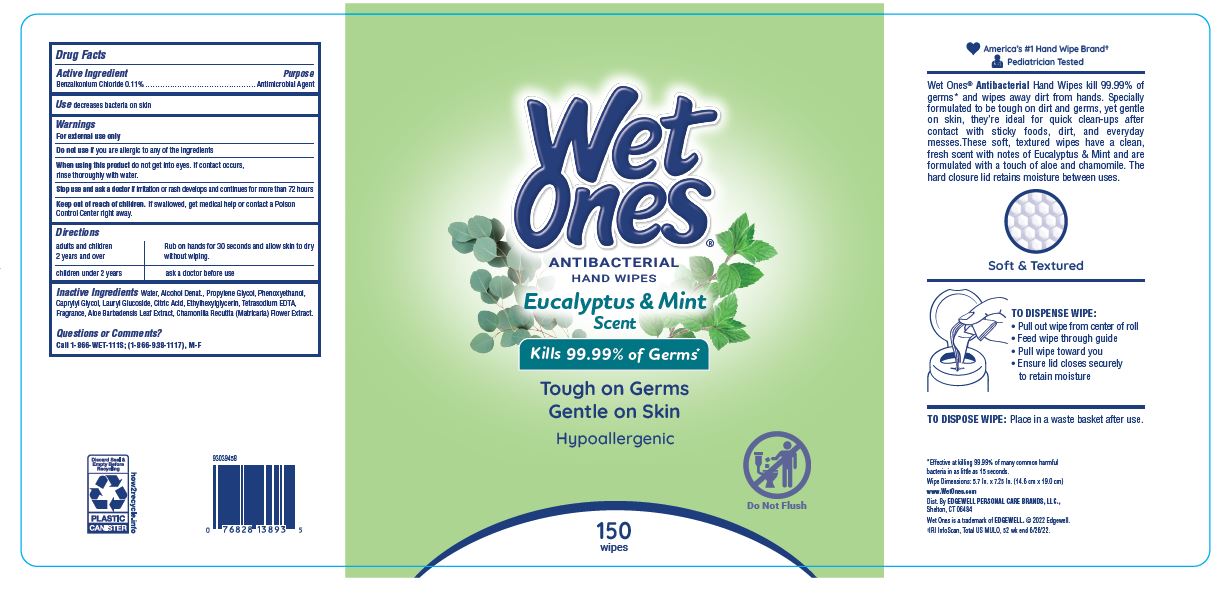 DRUG LABEL: Wet Ones Antibacterial Hand Wipes - Eucalyptus and Mint
NDC: 63354-547 | Form: SWAB
Manufacturer: Edgewell Personal Care Brands LLC
Category: otc | Type: HUMAN OTC DRUG LABEL
Date: 20251031

ACTIVE INGREDIENTS: BENZALKONIUM CHLORIDE 0.11 g/100 g
INACTIVE INGREDIENTS: PROPYLENE GLYCOL; ALOE VERA LEAF; WATER; EDETATE SODIUM; CITRIC ACID MONOHYDRATE; ETHYLHEXYLGLYCERIN; PHENOXYETHANOL; LAURYL GLUCOSIDE; DEHYDRATED ALCOHOL; CHAMOMILE; CAPRYLYL GLYCOL

Active Ingredient

Benzalkonium Chloride 0.11%

Purpose

Antimicrobial Agent

Use

decreases bacteria on skin

Warnings

For external use only

Do not use

if you are allergic to any of the ingredients

When using this product

do not get into eyes. If contact occurs, rinse thoroughly with water.

Stop use and ask a doctor

if irritation or rash develops and continues for more than 72 hours

Keep out of reach of children.

If swallowed, get medical help or contact a Poison Control Center right away.

Directions

adults and children 2 years and over - Rub on hands for 30 seconds and allow skin to dry without wiping.

children under 2 years - ask a doctor before use

Inactive Ingredients

Water, Alcohol Denat., Propylene Glycol, Phenoxyethanol, Caprylyl Glycol, Lauryl Glucoside, Citric Acid, Ethylhexylglycerin, Tetrasodium EDTA, Fragrance, Aloe Barbadensis Leaf Extract, Chamonilla Recutita (Matricaria) Flower Extract.

Questions or Comments?

Call 1-866-WET-111S; (1-866-938-1117), M-F

PRINCIPAL DISPLAY PANEL

WET

ONES

ANTIBACTERIAL

HAND WIPES

Eucalyptus & Mint

Kills 99.99% of Germs

Tough on Germs

Gentle on Skin

Hypoallergenic

Do Not Flush

150

wipes